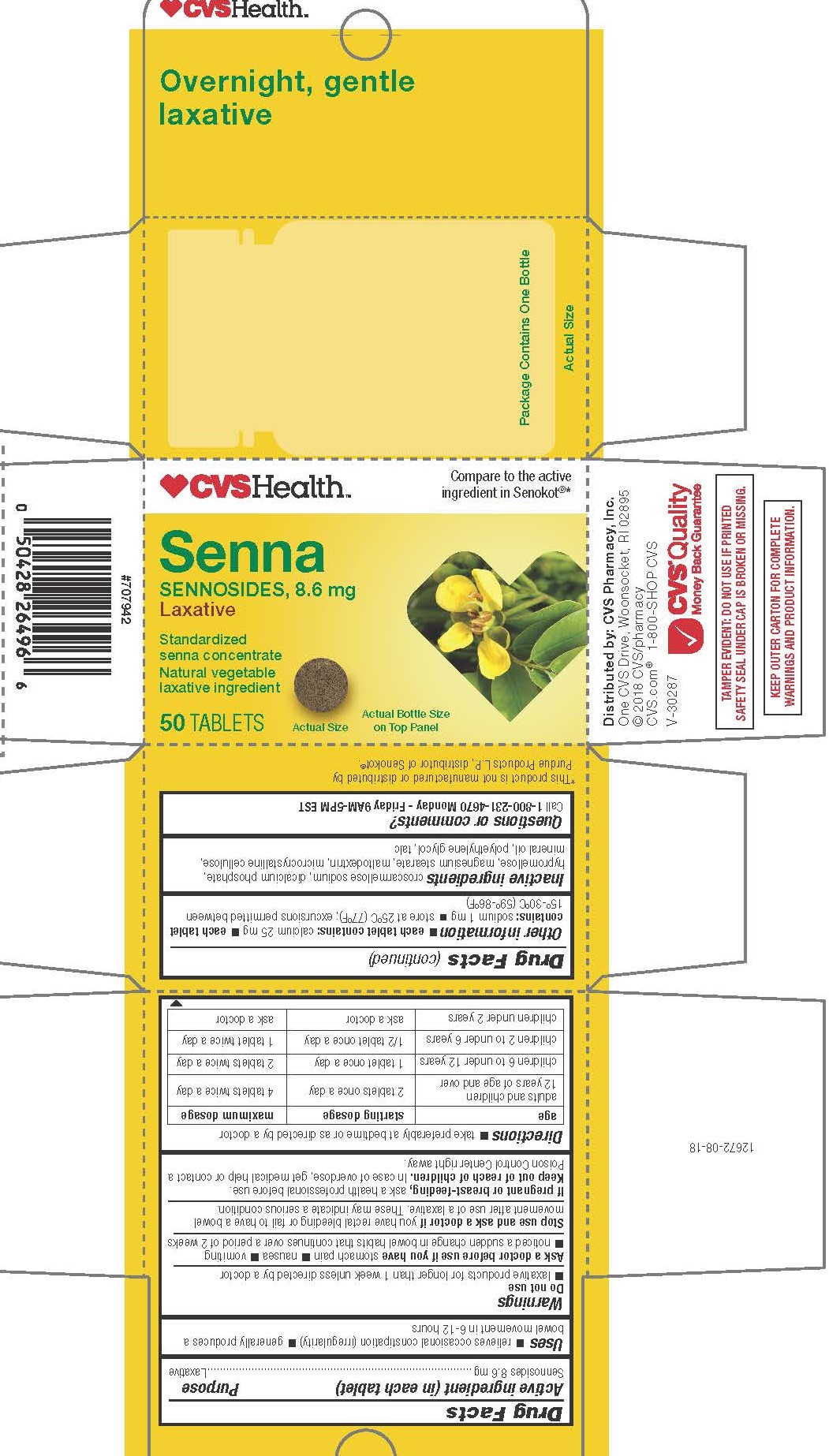 DRUG LABEL: SENNOSIDES
NDC: 69842-220 | Form: TABLET, FILM COATED
Manufacturer: CVS Pharmacy, Inc.
Category: otc | Type: HUMAN OTC DRUG LABEL
Date: 20241202

ACTIVE INGREDIENTS: SENNOSIDES 8.6 mg/1 1
INACTIVE INGREDIENTS: CROSCARMELLOSE SODIUM; HYPROMELLOSES; MAGNESIUM STEARATE; MALTODEXTRIN; MICROCRYSTALLINE CELLULOSE; LIGHT MINERAL OIL; POLYETHYLENE GLYCOL 400; TALC; CALCIUM PHOSPHATE, DIBASIC, DIHYDRATE

1122-CVS

Drug Facts

Active ingredient (in each tablet)

Sennosides 8.6 mg

PURPOSE

Laxative

Uses

- relieves occasional constipation (irregularity)
- generally produces a bowel movement in 6-12 hours

WARNINGS

Do not use laxative products for longer than 1 week unless directed by a doctor

Ask a doctor before use if you have

- stomach pain 
- nausea 
- vomiting
- noticed a sudden change in bowel habits that continues over a period of 2 weeks

Stop use and ask a doctor if you have rectal bleeding or fail to have a bowel movement after use of a laxative. These may indicate a serious condition.

PREGNANCY OR BREAST FEEDING

If pregnant or breast-feeding, ask a health professional before use.

Keep out of reach of children.

OVERDOSAGE

In case of overdose, get medical help or contact a Poison Control Center right away.

Directions

- take preferably at bedtime or as directed by a doctor

age | starting dosage | maximum dosage
adults and children; 12 years of age and over | 2 tablets once a day | 4 tablets twice a day
children 6 to under 12 years | 1 tablet once a day | 2 tablets twice a day
children 2 to under 6 years | 1/2 tablet once a day | 1 tablet twice a day
children under 2 years | ask a doctor | ask a doctor

Other information

 each tablet contains: calcium 20 mg

 store in a dry place at 15° – 30°C (59° – 86°F)

INACTIVE INGREDIENT

croscarmellose sodium, dicalcium phosphate, hypromellose, magnesium stearate, maltodextrin, microcrystalline cellulose, mineral oil, polyethylene glycol, talc

Questions or comments?

Call 1-877-753-3935 Monday - Friday 9AM-5PM EST

TAMPER EVIDENT: DO NOT USE IF PRINTED SAFETY SEAL UNDER CAP IS BROKEN OR MISSING.

KEEP OUTER CARTON FOR COMPLETE WARNINGS AND PRODUCT INFORMATION.

*This product is not manufactured or distributed by Avrio Health L.P., marketer of Senokot®.

Distributed by: CVS Pharmacy, Inc.
One CVS Drive, Woonsocket, RI 02895
© 2021 CVS/pharmacy
CVS.com® 1-800-SHOP CVS
V-30287

PACKAGE LABEL

CVSHealth

Compare to the active ingredient in Senokot®*

Senna

SENNOSIDES, 8.6 mg

Laxative

Standardized senna concentrate

Natural vegetable laxative ingredient

50 TABLETS